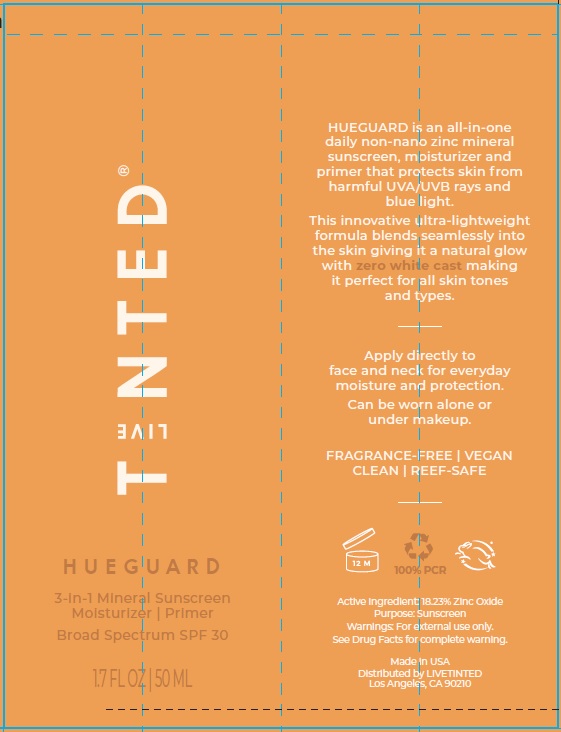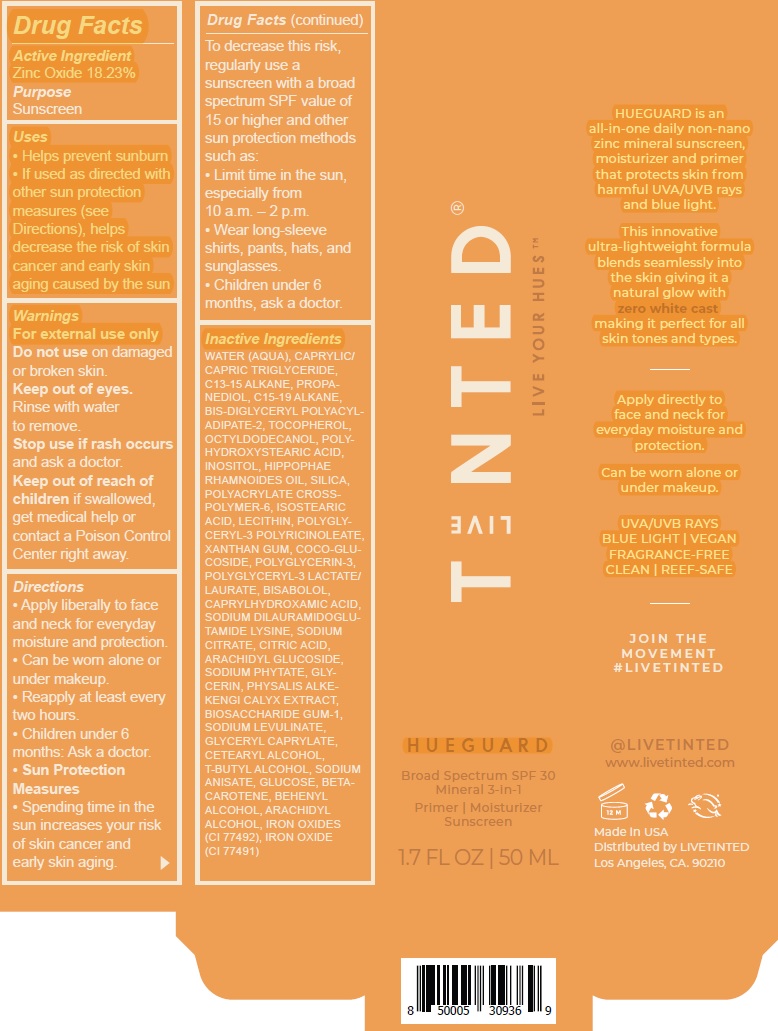 DRUG LABEL: Live Tinted Hueguard 3-in1 Mineral Sunscreen Moisturizer Primer Broad Spectrum SPF 30
NDC: 82153-001 | Form: CREAM
Manufacturer: Live Tinted, Inc.
Category: otc | Type: HUMAN OTC DRUG LABEL
Date: 20231028

ACTIVE INGREDIENTS: ZINC OXIDE 182.3 mg/1 mL
INACTIVE INGREDIENTS: WATER; MEDIUM-CHAIN TRIGLYCERIDES; C13-15 ALKANE; PROPANEDIOL; C15-19 ALKANE; BIS-DIGLYCERYL POLYACYLADIPATE-2; TOCOPHEROL; OCTYLDODECANOL; INOSITOL; SILICON DIOXIDE; AMMONIUM ACRYLOYLDIMETHYLTAURATE, DIMETHYLACRYLAMIDE, LAURYL METHACRYLATE AND LAURETH-4 METHACRYLATE COPOLYMER, TRIMETHYLOLPROPANE TRIACRYLATE CROSSLINKED (45000 MPA.S); ISOSTEARIC ACID; POLYGLYCERYL-3 PENTARICINOLEATE; XANTHAN GUM; COCO GLUCOSIDE; POLYGLYCERIN-3; LEVOMENOL; CAPRYLHYDROXAMIC ACID; SODIUM DILAURAMIDOGLUTAMIDE LYSINE; SODIUM CITRATE; CITRIC ACID MONOHYDRATE; ARACHIDYL GLUCOSIDE; HEXASODIUM PHYTATE; PHYTATE SODIUM; GLYCERIN; PHYSALIS ALKEKENGI CALYX; BIOSACCHARIDE GUM-1; SODIUM LEVULINATE; GLYCERYL CAPRYLATE; CETOSTEARYL ALCOHOL; TERT-BUTYL ALCOHOL; SODIUM ANISATE; ANHYDROUS DEXTROSE; BETA CAROTENE; DOCOSANOL; ARACHIDYL ALCOHOL; FERRIC OXIDE RED; FERRIC OXIDE YELLOW

Live Tinted Hueguard 3-in1 Mineral Sunscreen Moisturizer Primer Broad Spectrum SPF 30

Active Ingredient

Zinc Oxide 18.23%

Purpose

Sunscreen

Uses

- Helps prevent sunburn
- If used as directed with other sun protection measures (see Directions), helps decrease the risk of skin cancer and early skin aging caused by the sun

Warnings

For external use only

Do not use

on damaged or broken skin.

Rinse with water to remove. Keep out of eyes.

Stop use if rash occurs

and ask a doctor.

Keep out of reach of children

if swallowed, get medical help or contact a Poison Control Center right away.

Directions

• Apply liberally to face and neck for everyday moisture and protection. • Can be worn alone or under makeup. • Reapply at least every two hours. • Children under 6 months: Ask a doctor. • • Spending time in the sun increases your risk of skin cancer and early skin aging. To decrease this risk, regularly use a sunscreen with a broad spectrum SPF value of 15 or higher and other sun protection methods such as: • Limit time in the sun, especially from 10 a.m. – 2 p.m. • Wear long-sleeve shirts, pants, hats, and sunglasses. • Children under 6 months, ask a doctor.
Sun Protection Measures

Inactive Ingredients

WATER (AQUA), CAPRYLIC/ CAPRIC TRIGLYCERIDE, C13-15 ALKANE, PROPANEDIOL, C15-19 ALKANE, BIS-DIGLYCERYL POLYACYLADIPATE- 2, TOCOPHEROL, OCTYLDODECANOL, POLYHYDROXYSTEARIC ACID, INOSITOL, HIPPOPHAE RHAMNOIDES OIL, SILICA, POLYACRYLATE CROSSPOLYMER- 6, ISOSTEARIC ACID, LECITHIN, POLYGLYCERYL- 3 POLYRICINOLEATE, XANTHAN GUM, COCO-GLUCOSIDE, POLYGLYCERIN-3, POLYGLYCERYL-3 LACTATE/ LAURATE, BISABOLOL, CAPRYLHYDROXAMIC ACID, SODIUM DILAURAMIDOGLUTAMIDE LYSINE, SODIUM CITRATE, CITRIC ACID, ARACHIDYL GLUCOSIDE, SODIUM PHYTATE, GLYCERIN, PHYSALIS ALKEKENGI CALYX EXTRACT, BIOSACCHARIDE GUM-1, SODIUM LEVULINATE, GLYCERYL CAPRYLATE, CETEARYL ALCOHOL, T-BUTYL ALCOHOL, SODIUM ANISATE, GLUCOSE, BETACAROTENE, BEHENYL ALCOHOL, ARACHIDYL ALCOHOL, IRON OXIDES (CI 77492), IRON OXIDE (CI 77491)